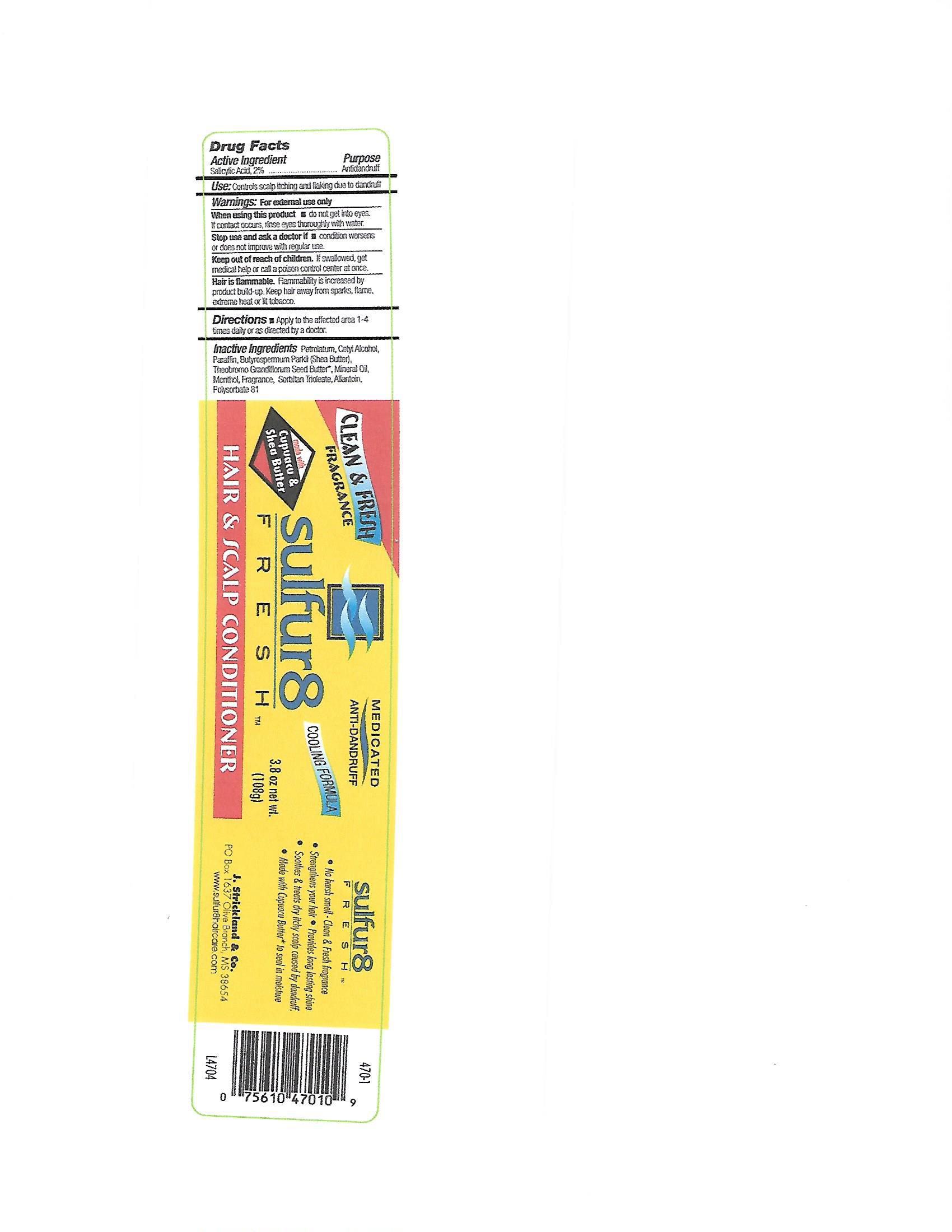 DRUG LABEL: Sulfur 8 Fresh Anti-Dandruff Hair and Scalp Conditioner
NDC: 12022-026 | Form: OINTMENT
Manufacturer: J. Strickland & Co.
Category: otc | Type: HUMAN OTC DRUG LABEL
Date: 20231021

ACTIVE INGREDIENTS: SALICYLIC ACID 20 mg/1 g
INACTIVE INGREDIENTS: PETROLATUM; CETYL ALCOHOL; PARAFFIN; SHEA BUTTER; THEOBROMA GRANDIFLORUM SEED BUTTER; MINERAL OIL; MENTHOL; SORBITAN TRIOLEATE; ALLANTOIN; POLYSORBATE 81

Sulfur 8 Fresh Anti-Dandruff Hair and Scalp Conditioner

Active Ingredients

Salicylic Acid, 2%

Purpose

Antidandruff

Use:

Controls scalp itching and flaking due to dandruff

Warnings:

For external use only

When using this product

- do not get into eyes. If contact occurs, rinse eyes thoroughly with water.

Stop use and ask a doctor if

- condition worsens or does not improve after regular use

Keep out of reach of children

If swallowed, get medical help or call a poison control center at once.

Directions

- Apply to the affected area 1-4 times daily, or as directed by a doctor.

Inactive Ingredients

Petrolatum, Cetyl Alcohol, Paraffin, Butyrospermum Parkii (Shea Butter), Theobromo Grandiflorum Seed Butter, Mineral Oil, Menthol, Fragrance, Sorbitan Trioleate, Allantion, Polysorbate 81